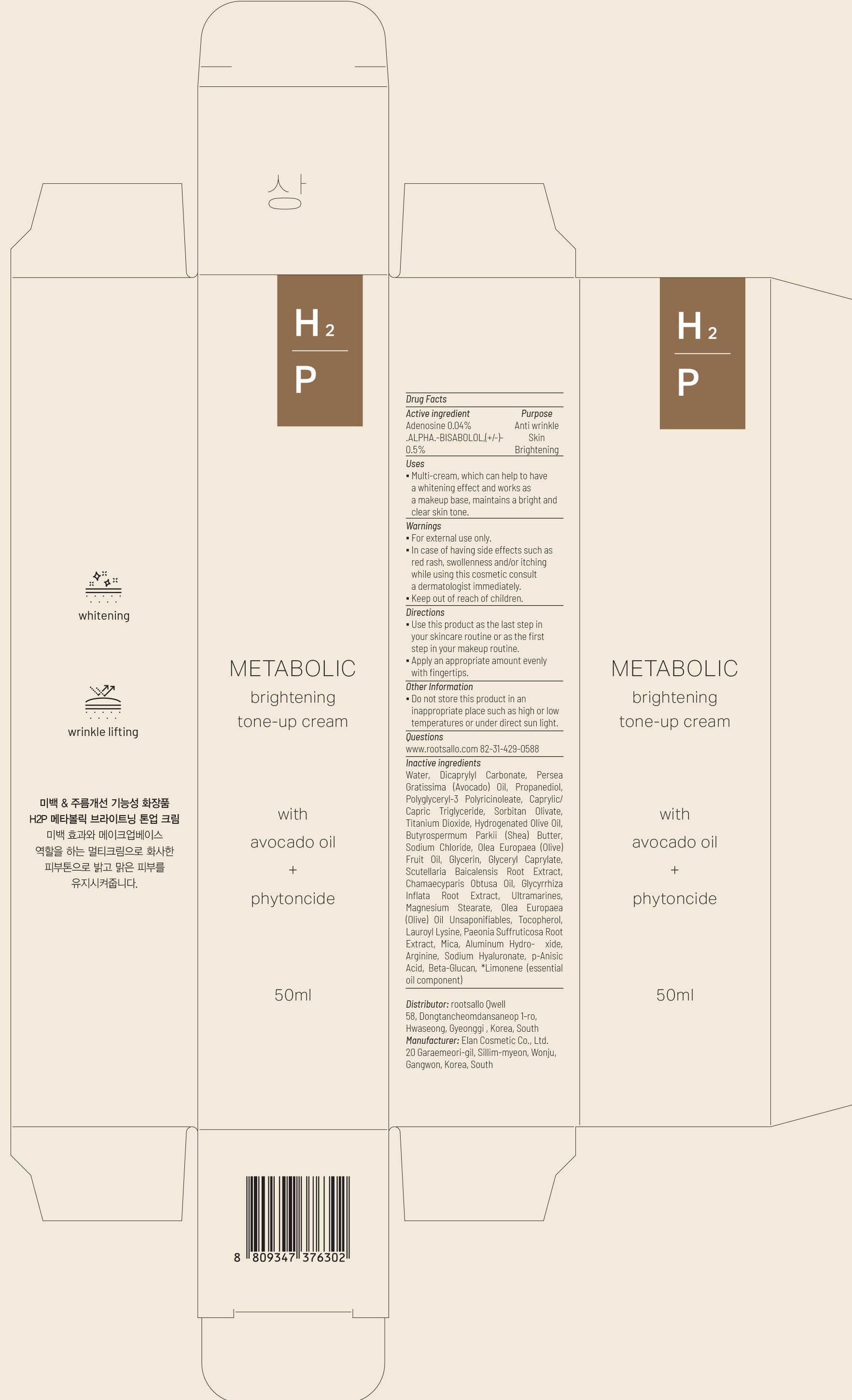 DRUG LABEL: METABOLIC BRIGHTENING TONE UP
NDC: 82450-030 | Form: CREAM
Manufacturer: rootsallo Qwell
Category: otc | Type: HUMAN OTC DRUG LABEL
Date: 20211230

ACTIVE INGREDIENTS: Adenosine 0.04 g/100 mL; .ALPHA.-BISABOLOL, (+/-)- 0.5 g/100 mL
INACTIVE INGREDIENTS: Water; Dicaprylyl Carbonate; AVOCADO OIL

ACTIVE INGREDIENTS

Adenosine 0.04%
.ALPHA.-BISABOLOL, (+/-)- 0.5%

PURPOSE

Anti wrinkle, Skin Brightening

Uses

Multi-cream, which can help to have a whitening effect and works as a makeup base, maintains a bright and clear skin tone.

Warnings

For external use only.
In case of having side effects such as red rash, swollenness and/or itching while using this cosmetic consult a dermatologist immediately.
Keep out of reach of children.

KEEP OUT OF REACH OF CHILDREN

Directions

Use this product as the last step in your skincare routine or as the first step in your makeup routine.
Apply an appropriate amount evenly with fingertips.

Other Information

Do not store this product in an inappropriate place such as high or low temperatures or under direct sun light.

Questions

www.rootsallo.com 82-31-429-0588

Inactive ingredients

Water, Dicaprylyl Carbonate, Persea Gratissima (Avocado) Oil, Propanediol, Polyglyceryl-3 Polyricinoleate, Caprylic/Capric Triglyceride, Sorbitan Olivate, Titanium Dioxide, Hydrogenated Olive Oil, Butyrospermum Parkii (Shea) Butter, Sodium Chloride, Olea Europaea (Olive) Fruit Oil, Glycerin, Glyceryl Caprylate, Scutellaria Baicalensis Root Extract, Chamaecyparis Obtusa Oil, Glycyrrhiza Inflata Root Extract, Ultramarines, Magnesium Stearate, Olea Europaea (Olive) Oil Unsaponifiables, Tocopherol, Lauroyl Lysine, Paeonia Suffruticosa Root Extract, Mica, Aluminum Hydroxide, Arginine, Sodium Hyaluronate, p-Anisic Acid, Beta-Glucan, *Limonene (essential oil component)